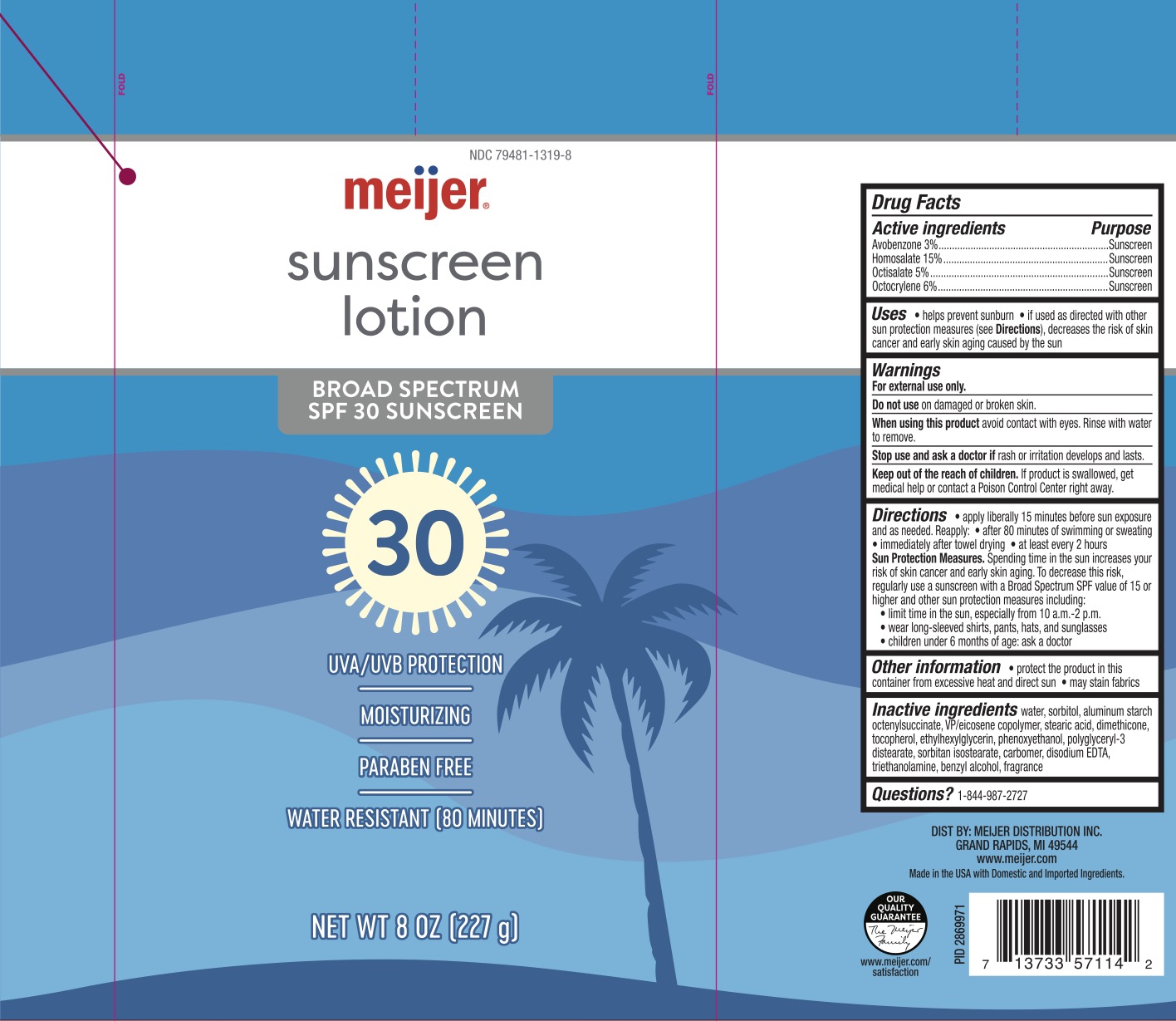 DRUG LABEL: Meijer SPF 30 Sunscreen
NDC: 79481-1319 | Form: LOTION
Manufacturer: Meijer
Category: otc | Type: HUMAN OTC DRUG LABEL
Date: 20240219

ACTIVE INGREDIENTS: OCTOCRYLENE 6 g/100 g; AVOBENZONE 3 g/100 g; HOMOSALATE 15 g/100 g; OCTISALATE 5 g/100 g
INACTIVE INGREDIENTS: PHENOXYETHANOL; ETHYLHEXYLGLYCERIN; TOCOPHEROL; SORBITOL; STEARIC ACID; EICOSYL POVIDONE; DIMETHICONE 200; TROLAMINE; EDETATE DISODIUM; ALUMINUM STARCH OCTENYLSUCCINATE; CARBOMER 940; WATER; POLYGLYCERYL-3 DISTEARATE; SORBITAN ISOSTEARATE; BENZYL ALCOHOL

Meijer SPF 30 Sunscreen Lotion

ACTIVE INGREDIENT

Avobenzone 3%, Homosalate 15%, Octisalate 5%, Octocrylene 6%

PURPOSE

Sunscreen

INDICATIONS AND USAGE

Helps prevent sunburn.

If used as directed with other sun protection measures (see Directions), decreases the risk of skin cancer and early skin aging caused by the sun.

WARNINGS

For external use only.

Do not use on damaged or broken skin.

When using this product avoid contact with eyes. Rinse with water to remove.

Stop use and ask a doctor if rash or irritation develops and lasts.

KEEP OUT OF REACH OF CHILDREN

If product is swallowed, get medical help or contact a Poison Control Center right away.

DOSAGE AND ADMINISTRATION

Apply liberally 15 minutes before sun exposure. Reapply: after 80 minutes of swimming or sweating, immediately after towel drying, at least every 2 hours.

Sun Protection Measures. Spending time in the sun increases your risk of skin cancer and early skin aging. To decrease this risk, regularly use a sunscreen with a Broad Spectrum SPF value of 15 or higher and other sun protection measures including: limit time in the sun, especially from 10 a.m. - 2 p.m., wear long-sleeved shirts, pants, hats, and sunglasses, children under 6 months of age: ask a doctor, hold container 4 to 6 inches from the skin to apply, do not spray directly onto face Spray onto hand then apply to face, do not apply in windy conditions, use in well-ventilated area.

INACTIVE INGREDIENT

Water, sorbitol, aluminum starch octenylsuccinate, VP/Eicosene copolymer, stearic acid, dimethicone, tocopherol, ethylhexylglycerin, phenoxyethanol, polyglyceryl-3 distearate, sorbitan isostearate, carbomer, disodium EDTA, triethanolamine, benzyl alcohol, fragrance.